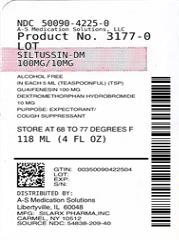 DRUG LABEL: Siltussin DM
NDC: 50090-4225 | Form: LIQUID
Manufacturer: A-S Medication Solutions
Category: otc | Type: HUMAN OTC DRUG LABEL
Date: 20190329

ACTIVE INGREDIENTS: GUAIFENESIN 100 mg/5 mL; DEXTROMETHORPHAN HYDROBROMIDE 10 mg/5 mL
INACTIVE INGREDIENTS: ANHYDROUS CITRIC ACID; FD&C RED NO. 40; GLYCERIN; MENTHOL, UNSPECIFIED FORM; METHYLPARABEN; PROPYLENE GLYCOL; SACCHARIN SODIUM; SODIUM BENZOATE; SUCROSE; WATER

Siltussin DM Cough Syrup

Active Ingredient: Guaifenesin 100 mg (in each 5 mL (teaspoon)(TSP))

Active Ingredient: Dextromethorphan Hydrobromide 10 mg (in each 5 mL (teaspoon)(TSP))

Purpose of Guaifenesin: Expectorant

Purpose of Dextromethorphan Hydrobromide: Cough Suppressant

Uses

- temporarily relieves cough due to minor throat and bronchial irritation
- helps loosen phlegm (mucus) and thin bronchial secretions to make coughs more productive

Warnings

Do not use if you are now taking a prescription monoamine oxidase inhibitor (MAOI) (certain drugs for depression, psychiatric or emotional conditions, or Parkinson’s disease), or for 2 weeks after stopping the MAOI drug. If you do not know if your prescription drug contains an MAOI, ask a doctor or pharmacist before taking this product.

Ask a doctor before use if you have

- persistent cough or chronic cough such as occurs with smoking, asthma, chronic bronchitis, emphysema
- cough accompanied by excessive phlegm (mucus)

Stop use and ask a doctor if

- cough lasts more than 7 days or occurs with fever, rash, or headaches that lasts. This could be signs of a serious condition
- hypersensitive to any ingredients

If pregnant or breast-feeding

- ask a health professional before use.

Keep out of reach of children. In case of overdose, get medical help or contact a Poison Control Center right away.

Directions

do not take more than 6 doses in any 24-hour period. This adult product is not intended for use in children under 12 years of age

Adults and children 12 years and over | 2 teaspoonfuls (TSP) every 4 hours
Children under 12 years | DO NOT USE

Inactive ingredients

citric acid, FD&C red no. 40, glycerin, menthol, methylparaben, propylene glycol, saccharin sodium, sodium benzoate, strawberry flavor, sucrose, purified water.

Other information

store at room temperature 20°-25°C (68°-77°F)

Questions: 888-974-5279

Manufactured by

Silarx Pharmaceutical Inc,

1033 Stoneleigh Ave.
Carmel, NY 10512

HOW SUPPLIED

Product: 50090-4225

NDC: 50090-4225-0 118 mL in a BOTTLE, PLASTIC